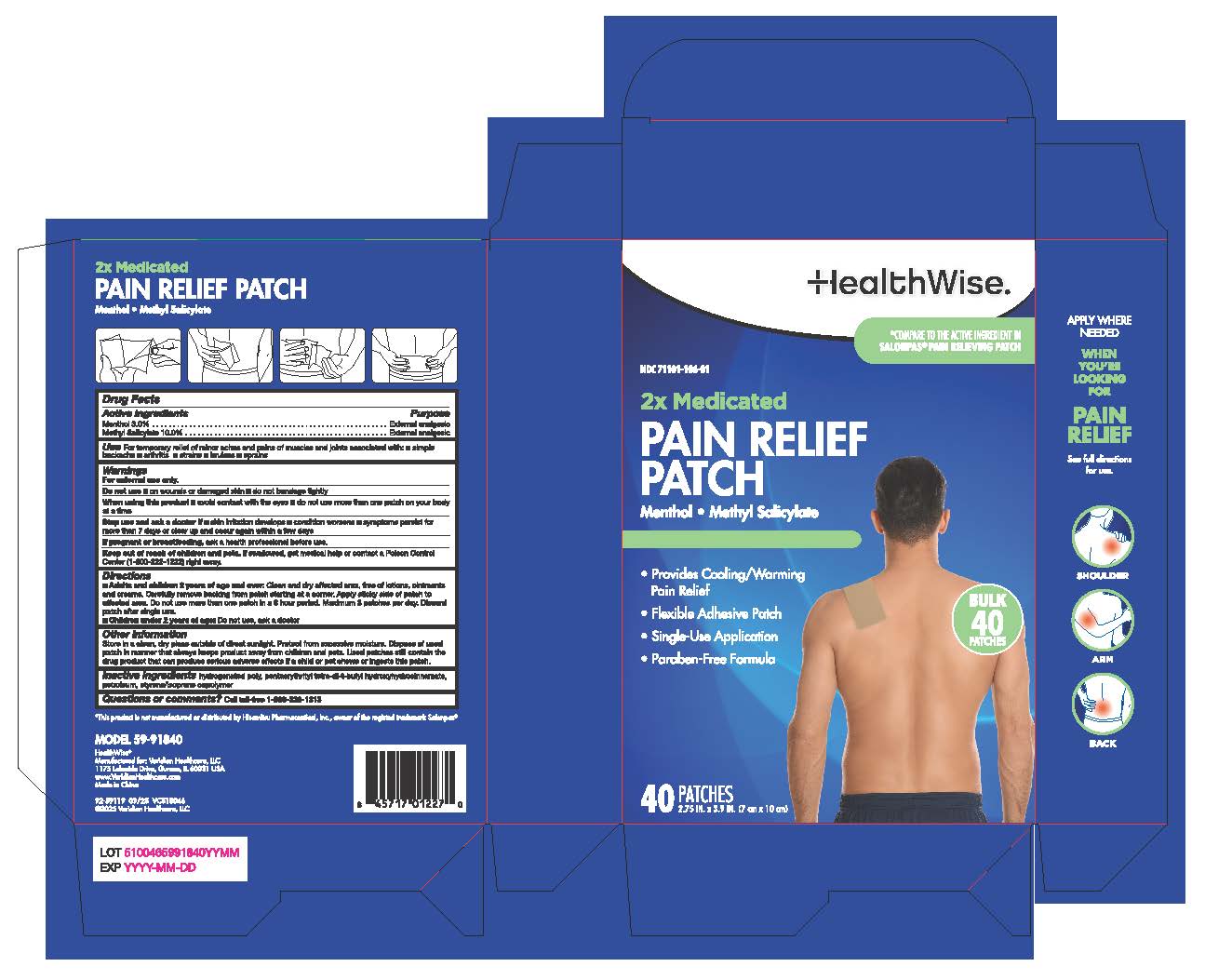 DRUG LABEL: HealthWise Pain Relief Patch
NDC: 71101-106 | Form: PATCH
Manufacturer: Veridian Healthcare
Category: otc | Type: HUMAN OTC DRUG LABEL
Date: 20251007

ACTIVE INGREDIENTS: MENTHOL 3 g/100 g; METHYL SALICYLATE 10 g/100 g
INACTIVE INGREDIENTS: HYDROGENATED C6-20 POLYOLEFIN (100 CST); PENTAERYTHRITOL TETRAKIS(3-(3,5-DI-TERT-BUTYL-4-HYDROXYPHENYL)PROPIONATE); LIQUID PETROLEUM; STYRENE/ISOPRENE COPOLYMER (28:72; 210000 MW)

HealthWise Pain Relief Patch

Active Ingredients

Active Ingredients Purpose

Menthol 3.0% .......................External Analgesic

Methyl Salicylate 10.0% .......External Analgesic

Warnings

For External Use Only

Do not use:

- on wounds or damaged skin ■ do not bandage tightly

When using this product

- avoid contact with eyes ■ Do not use more than one patch on your body at a time

Stop use and consult a doctor

Stop use and ask a doctor if■ skin irritation develops ■ condition worsens ■ symptoms persist for more than 7 days or clear up and occur again within a few days

Keep out of reach of children

If swallowed, get medical help or contact a Poison Control Center (1-800-222-1222) right away.

Purpose

External Analgesic

Directions

■Adults and children 2 years of age and over: Clean and dry affected area, free of lotions, ointments and creams. Carefully remove backing from patch starting at a corner. Apply sticky side of patch to affected area. Do not use more than one patch in a 8 hour period. Maximum 3 patches per day. Discardpatch after single use.

■ Children under 2 years of age: Do not use, ask a doctor

Inactive Ingredients

Hydrogenated Poly, Pentaerythrityl Tetra-di-t-butyl Hydroxyhydrocinnamate, Petroleum, Styrene / Isoprene Copolymer

Indication and Usage

Temporarily relieves mild to moderate aches and pains of muscles and joints associated with:
■ strains ■ sprains ■ simple backache ■ arthritis ■ bruises

If pregnant or breastfeeding

ask a health professional before use

Questions or Comments?

Toll Free 1-866-326-1313

Other information

■ store at 20-25°C (68-77°F) ■ avoid storing in direct sunlight ■ protect product from excessive moisture ■ some individuals may not experience pain relief until several hours after applying the patch